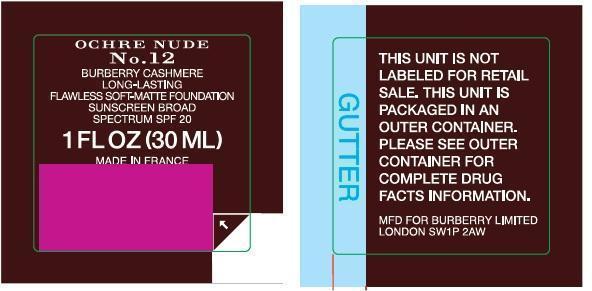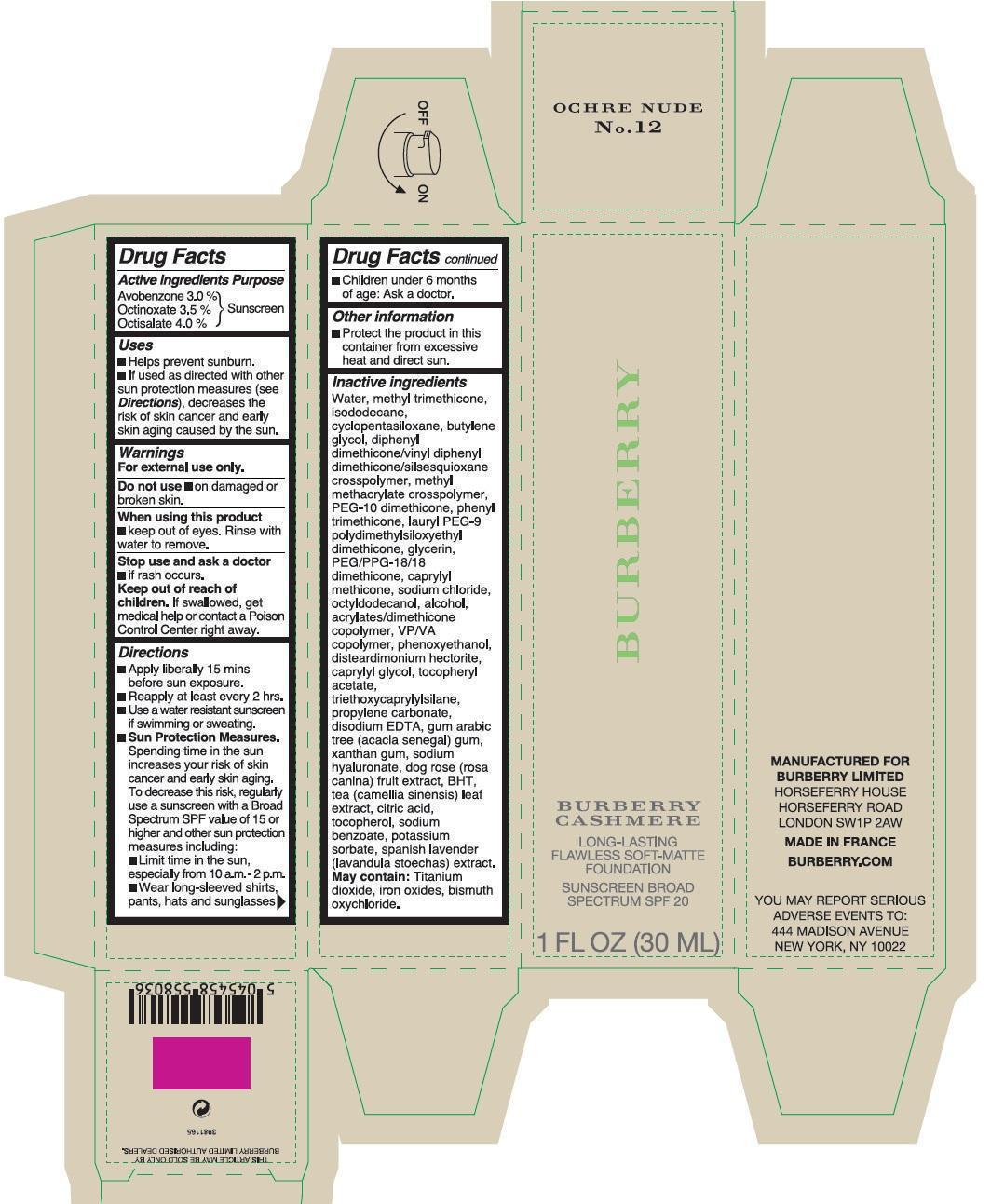 DRUG LABEL: Burberry Cashmere Long-Lasting Flawless Soft-Matte Foundation Sunscreen Broad Spectrum SPF 20 Ochre Nude No.12
NDC: 69038-027 | Form: CREAM
Manufacturer: Burberry Limited
Category: otc | Type: HUMAN OTC DRUG LABEL
Date: 20171228

ACTIVE INGREDIENTS: AVOBENZONE 30 mg/1 mL; OCTINOXATE 35 mg/1 mL; OCTISALATE 40 mg/1 mL
INACTIVE INGREDIENTS: WATER; METHYL TRIMETHICONE; ISODODECANE; CYCLOMETHICONE 5; BUTYLENE GLYCOL; PHENYL TRIMETHICONE; LAURYL PEG-9 POLYDIMETHYLSILOXYETHYL DIMETHICONE; GLYCERIN; PEG/PPG-18/18 DIMETHICONE; CAPRYLYL TRISILOXANE; SODIUM CHLORIDE; OCTYLDODECANOL; ALCOHOL; COPOVIDONE K25-31; PHENOXYETHANOL; DISTEARDIMONIUM HECTORITE; CAPRYLYL GLYCOL; .ALPHA.-TOCOPHEROL ACETATE; TRIETHOXYCAPRYLYLSILANE; PROPYLENE CARBONATE; EDETATE DISODIUM; ACACIA; XANTHAN GUM; HYALURONATE SODIUM; TEA LEAF; CITRIC ACID MONOHYDRATE; TOCOPHEROL; SODIUM BENZOATE; POTASSIUM SORBATE; LAVANDULA STOECHAS FLOWERING TOP; TITANIUM DIOXIDE; FERRIC OXIDE RED; BISMUTH OXYCHLORIDE

Burberry Cashmere Long-Lasting Flawless Soft-Matte Foundation Sunscreen Broad Spectrum SPF 20 Ochre Nude No.12

Active ingredients

Avobenzone 3.0%

Octinoxate 3.5%

Octisalate 4%

Purpose

Sunscreen

Uses

- Helps prevent sunburn.
- If used as directed with other sun protection measures (see Directions), decreases the risk of skin cancer and early skin aging caused by the sun.

Warnings

For external use only.

Do not use

- on damaged or broken skin.

When using this product

- keep out of eyes. Rinse with water to remove.

Stop use and ask a doctor

- if rash occurs.

Keep out of reach of children.

If swallowed, get medical help or contact a Poison Control Center right away.

Directions

- Apply liberally 15 mins before sun exposure.
- Reapply at least every 2 hrs.
- Use a water resistant sunscreen if swiming or sweating.
- Sun Protection Measures. Spending time in the sun increases your risk of skin cancer and early skin aging. To decrease this risk, regularly use a sunscreen with a Broad Spectrum SPF value of 15 or higher and other sun protection measures including:
- Limit time in the sun, especially from 10 a.m. - 2 p.m.
- Wear long-sleeved shirts, pants, hats and sunglasses
- Children under 6 months of age: Ask doctor.

Other information

- Protect the product in this container from excessive heat and direct sun.

Inactive ingredients

Water, methyl trimethicone, isododecane, cyclopentasiloxane, butylene glycol, diphenyl dimethicone/vinyl diphenyl dimethicone/vinyl diphenyl dimethicone/silsesquioxane cross polymer, methyl methacrylate crosspolymer, PEG-10 dimethicone, phenyl trimethicone, lauryl PEG-9 polydimethylsiloxyethyl dimethicone, glycerin, PEG/PPG-18/18 dimethicone, caprylyl methicone, sodium chloride, octyldodecanol, alcohol, acrylates/dimethicone copolymer, VP/VA copolymer, phenoxyethanol, disteardimonium hectorite, caprylyl glycol, tocopheryl acetate, triethoxycaprylylsilane, propylene carbonate, disodium EDTA, gum arabic tree (acacia senegal) gum, xanthan gum, sodium hyaluronate, dog rose (rosa canina) fruit extract, BHT, tea (camellia sinensis) leaf extract, citric acid, tocopherol, sodium benzoate, potassium sorbate, spanish lavender (lavandula stoechas) extract. May contain: Titanium dioxide, iron oxides, bismuth oxycholride.